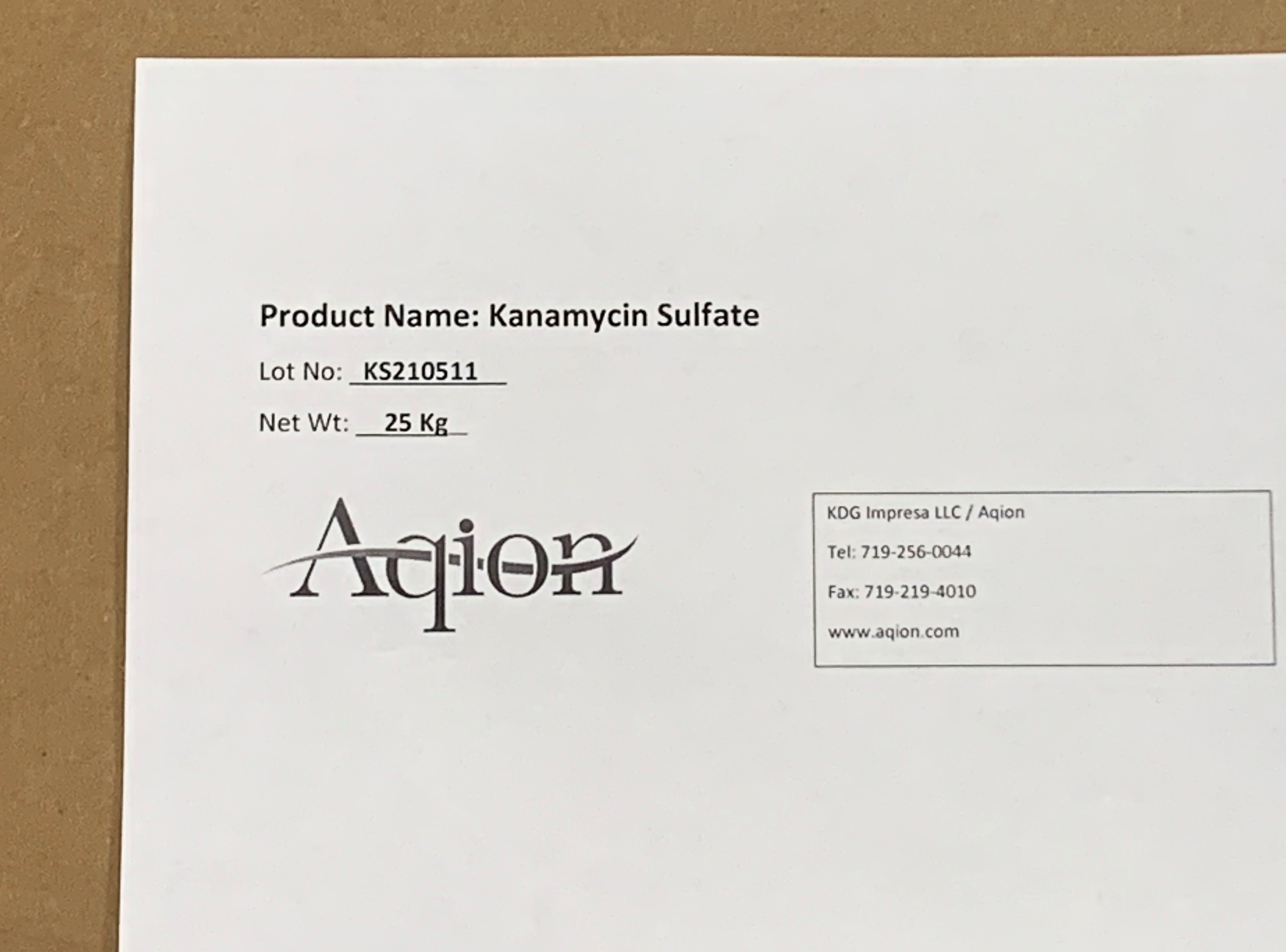 DRUG LABEL: Kanamycin Sulfates
NDC: 43457-527 | Form: POWDER
Manufacturer: KDG Impresa LLC, Aqion
Category: other | Type: BULK INGREDIENT - ANIMAL DRUG
Date: 20220130

ACTIVE INGREDIENTS: KANAMYCIN SULFATES 1 kg/1 kg

Kanamycin Sulfate